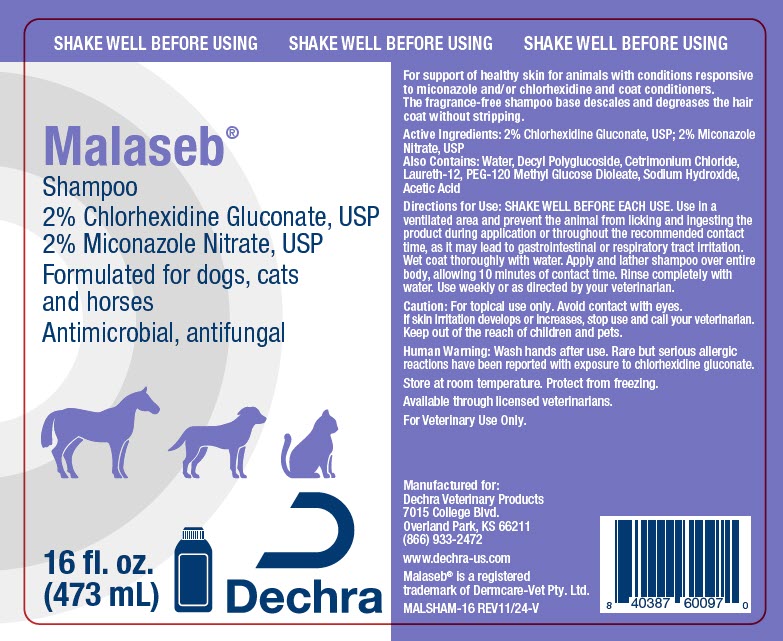 DRUG LABEL: Malaseb
NDC: 17033-185 | Form: SHAMPOO
Manufacturer: Dechra Veterinary Products
Category: animal | Type: OTC ANIMAL DRUG LABEL
Date: 20241212

ACTIVE INGREDIENTS: CHLORHEXIDINE GLUCONATE 20 mg/1 mL; MICONAZOLE NITRATE 20 mg/1 mL

Malaseb® Shampoo

VETERINARY INDICATIONS

For support of healthy skin for animals with conditions responsive to miconazole and/or chlorhexidine and coat conditioners.

The fragrance-free shampoo base descales and degreases the hair coat without stripping.

DESCRIPTION

Active Ingredients: 2% Chlorhexidine Gluconate, USP; 2% Miconazole Nitrate, USP

Also Contains: Water, Decyl Polyglucoside, Cetrimonium Chloride, Laureth-12, PEG-120 Methyl Glucose Dioleate, Sodium Hydroxide, Acetic Acid

DOSAGE AND ADMINISTRATION

Directions for Use: SHAKE WELL BEFORE EACH USE. Use in a ventilated area and prevent the animal from licking and ingesting the product during application or throughout the recommended contact time, as it may lead to gastrointestinal or respiratory tract irritation.

Wet coat thoroughly with water. Apply and lather shampoo over entire body, allowing 10 minutes of contact time. Rinse completely with water. Use weekly or as directed by your veterinarian.

PRECAUTIONS

Caution: For topical use only. Avoid contact with eyes. If skin irritation develops or increases, stop use and call your veterinarian. Keep out of the reach of children and pets.

SAFE HANDLING WARNING

Human Warning: Wash hands after use. Rare but serious allergic reactions have been reported with exposure to chlorhexidine gluconate.

STORAGE AND HANDLING

Store at room temperature. Protect from freezing.

Available through licensed veterinarians.

For Veterinary Use Only.

Manufactured for:
Dechra Veterinary Products
7015 College Blvd.
Overland Park, KS 66211
(866) 933-2472

www.dechra-us.com

Malaseb® is a registered
trademark of Dermcare-Vet Pty. Ltd.

MALSHAM-16 REV11/24-V

PRINCIPAL DISPLAY PANEL - 473 mL Bottle Label

SHAKE WELL BEFORE USING

Malaseb®
Shampoo
2% Chlorhexidine Gluconate, USP
2% Miconazole Nitrate, USP
Formulated for dogs, cats
and horses
Antimicrobial, antifungal

16 fl. oz.
(473 mL)

Dechra